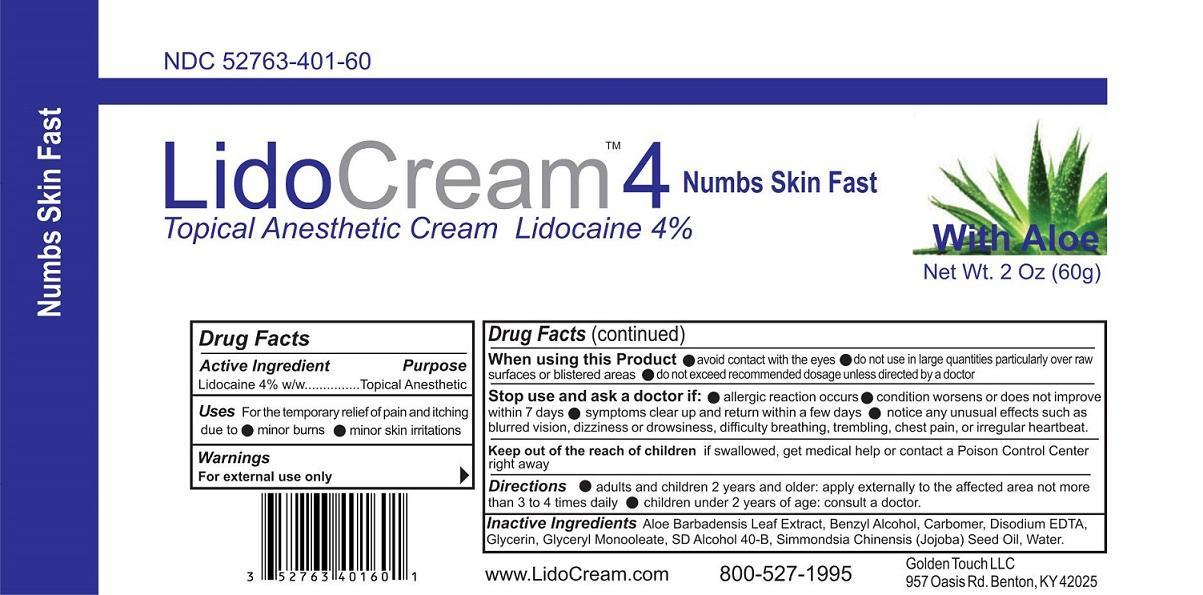 DRUG LABEL: LidoCream 4
NDC: 52763-401 | Form: CREAM
Manufacturer: Golden Touch LLC
Category: otc | Type: HUMAN OTC DRUG LABEL
Date: 20151111

ACTIVE INGREDIENTS: LIDOCAINE 4 g/100 g
INACTIVE INGREDIENTS: ALOE VERA LEAF; BENZYL ALCOHOL; CARBOMER HOMOPOLYMER TYPE C (ALLYL PENTAERYTHRITOL CROSSLINKED); EDETATE DISODIUM; GLYCERIN; GLYCERYL OLEATE; ALCOHOL; SIMMONDSIA CHINENSIS SEED; WATER

LidoCream 4

Active ingredient

Lidocaine 4% W/W

Purpose

Topical Anesthetic

Keep out of reach of children. If swallowed, get medical help or contact a Poison Control Center right away.

Uses

For the temporary relief of pain and itching due to

- minor burns
- minor skin irritations

Warnings

For external use only

When using this product

- Avoid contact with the eyes
- Do not use in large quantities particularly over raw surfaces or blistered areas.
- Do not exceed recommended dosage unless directed by a doctor

Stop use and ask a doctor if

- allergic reaction occurs
- condition worsens or does not improve within 7 days
- Symptoms clear up and return within a few days
- notice any unusual effects such as blurred vision, dizziness or drowsiness, difficulty in breathing, trembling, chest pain or irregular heart beat

Directions

- Adults and children 2 years and older: apply externally to the affected area not more than 3 to 4 times daily
- Children under 2 years of age: consult a doctor

Inactive ingredients

Aloe Barbadensis Leaf Extract, Benzyl Alcohol, Carbomer, Disodium EDTA, Glycerin, Glyceryl Monooleate, SD Alcohol 40-B, Simmondsia Chinensis (Jojoba) Seed Oil, Water